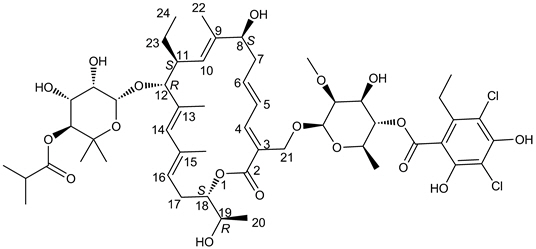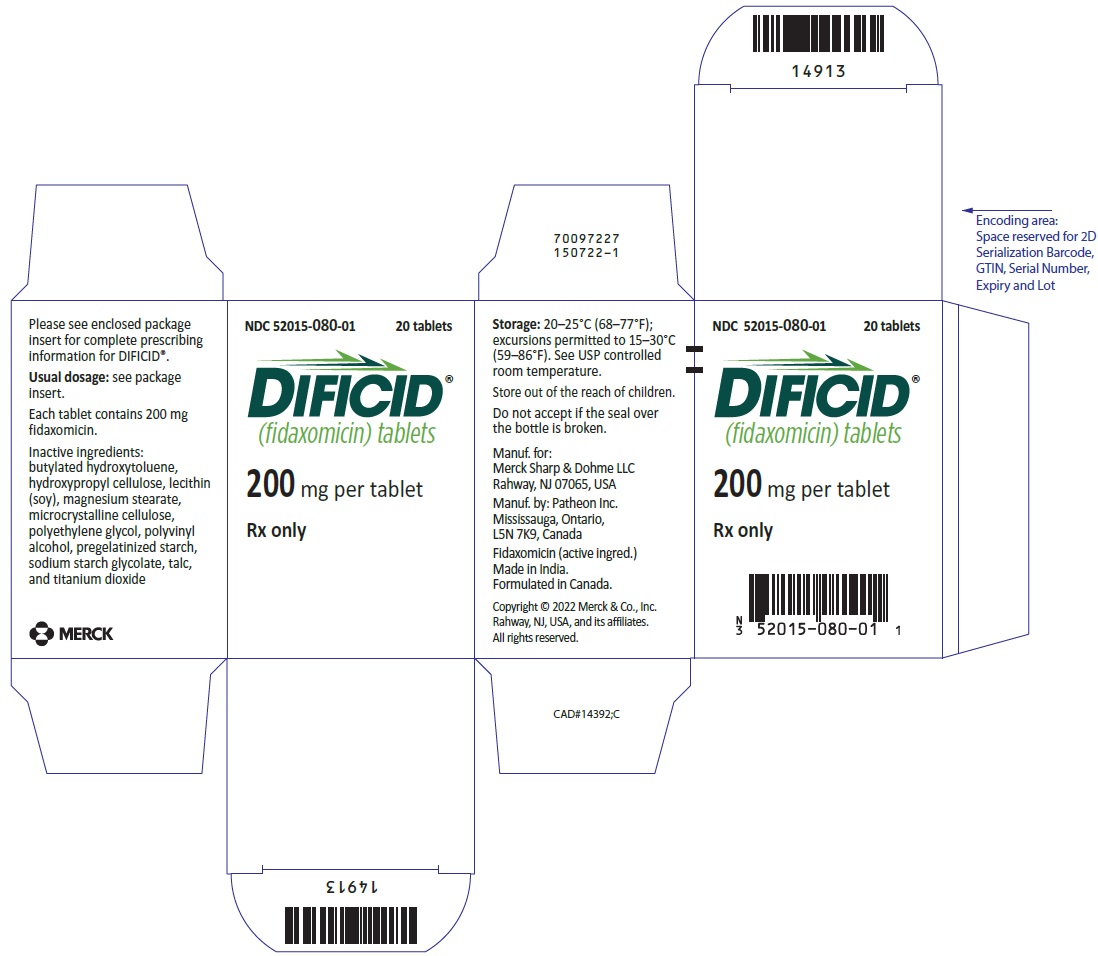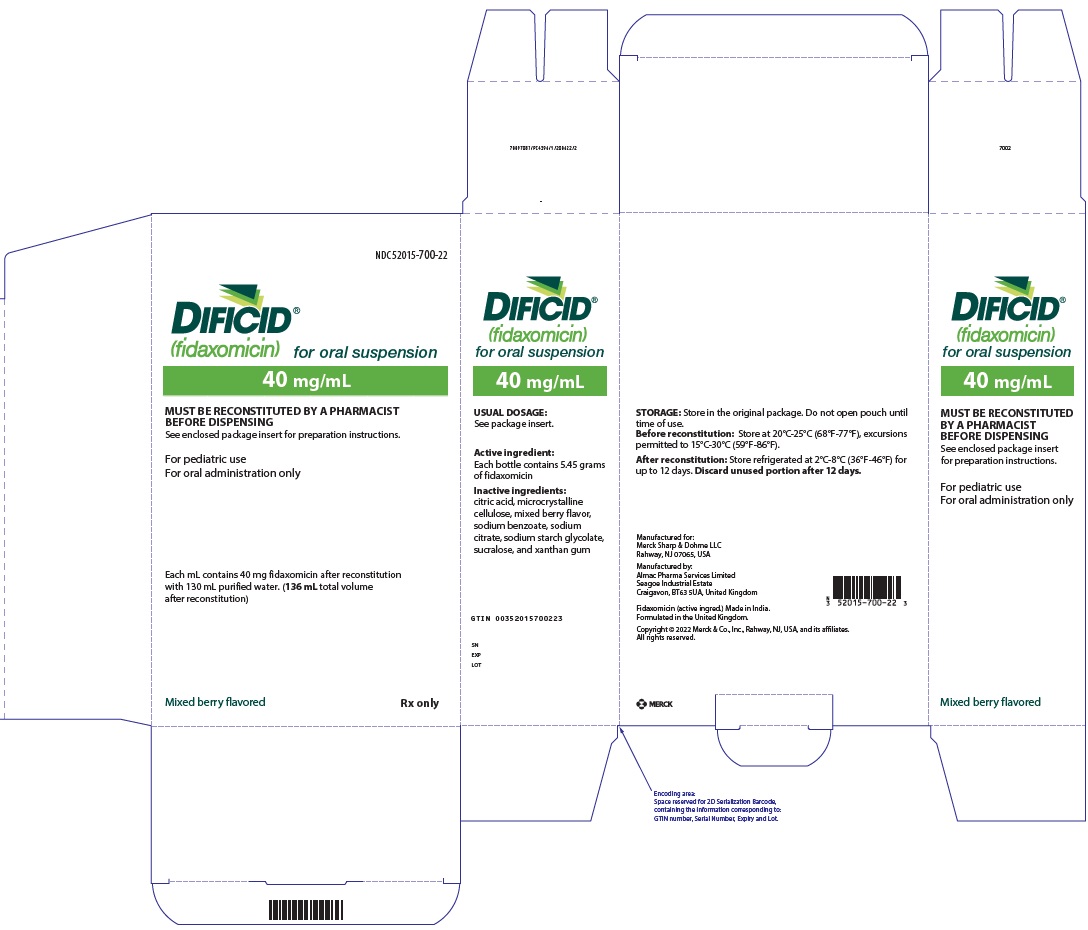 DRUG LABEL: Dificid
NDC: 52015-080 | Form: TABLET, FILM COATED
Manufacturer: Merck Sharp & Dohme LLC
Category: prescription | Type: HUMAN PRESCRIPTION DRUG LABEL
Date: 20241016

ACTIVE INGREDIENTS: FIDAXOMICIN 200 mg/1 1
INACTIVE INGREDIENTS: MICROCRYSTALLINE CELLULOSE; STARCH, CORN; HYDROXYPROPYL CELLULOSE (1600000 WAMW); BUTYLATED HYDROXYTOLUENE; SODIUM STARCH GLYCOLATE TYPE A POTATO; MAGNESIUM STEARATE; POLYVINYL ALCOHOL, UNSPECIFIED; TITANIUM DIOXIDE; TALC; POLYETHYLENE GLYCOL, UNSPECIFIED; LECITHIN, SOYBEAN

HIGHLIGHTS OF PRESCRIBING INFORMATION

These highlights do not include all the information needed to use DIFICID safely and effectively. See full prescribing information for DIFICID.
DIFICID® (fidaxomicin) tablets, for oral use
DIFICID® (fidaxomicin) for oral suspension
Initial U.S. Approval: 2011

1 INDICATIONS AND USAGE

DIFICID is a macrolide antibacterial indicated in adult and pediatric patients 6 months of age and older for the treatment of C. difficile-associated diarrhea. (1.1)

To reduce the development of drug-resistant bacteria and maintain the effectiveness of DIFICID and other antibacterial drugs, DIFICID should be used only to treat infections that are proven or strongly suspected to be caused by C. difficile. (1.2)

2 DOSAGE AND ADMINISTRATION

- DIFICID is administered orally with or without food. (2.1)
- Adults
  - One 200 mg tablet orally twice daily for 10 days. (2.2)
- Pediatrics (6 Months to Less than 18 Years of Age)
- Tablets
  - Pediatric patients weighing at least 12.5 kg and able to swallow tablets: One 200 mg tablet orally twice daily for 10 days. (2.3)
- Oral Suspension
  - Pediatric patients weighing at least 4 kg: Weight-based dosing of the oral suspension twice daily for 10 days using an oral dosing syringe, as specified in Table 1 in the full prescribing information. (2.3)
  - For instructions on preparation and administration of DIFICID oral suspension, see full prescribing information. (2.4)

3 DOSAGE FORMS AND STRENGTHS

- Film-coated tablets: 200 mg (3)
- For oral suspension: 40 mg/mL (200 mg/5 mL) when reconstituted (3)

4 CONTRAINDICATIONS

DIFICID is contraindicated in patients who have known hypersensitivity to fidaxomicin or any other ingredient in DIFICID. (4)

5 WARNINGS AND PRECAUTIONS

- Acute hypersensitivity reactions (angioedema, dyspnea, pruritus, and rash) have been reported. If a severe hypersensitivity reaction occurs, discontinue DIFICID. (5.1)
- DIFICID is not expected to be effective for the treatment of other types of infections due to minimal systemic absorption of fidaxomicin. DIFICID should only be used for the treatment of C. difficile-associated diarrhea. (5.2)
- Development of drug-resistant bacteria: Only use DIFICID for infection proven or strongly suspected to be caused by C. difficile. (5.3)

6 ADVERSE REACTIONS

The most common adverse reactions in adults (incidence ≥2%) are nausea, vomiting, abdominal pain, gastrointestinal hemorrhage, anemia, and neutropenia. (6)

The most common adverse reactions in pediatric patients (incidence ≥5%) treated with DIFICID are pyrexia, abdominal pain, vomiting, diarrhea, constipation, increased aminotransferases, and rash. (6)

To report SUSPECTED ADVERSE REACTIONS, contact Merck Sharp & Dohme LLC at 1-877-888-4231 or FDA at 1-800-FDA-1088 or www.fda.gov/medwatch .

8 USE IN SPECIFIC POPULATIONS

Pediatrics: The safety and effectiveness of DIFICID have not been established in pediatric patients younger than 6 months of age. (8.4)

FULL PRESCRIBING INFORMATION

1 INDICATIONS AND USAGE

1.1 Clostridioides difficile-Associated Diarrhea

DIFICID® is indicated in adult and pediatric patients aged 6 months and older for the treatment of C. difficile-associated diarrhea (CDAD).

1.2 Usage

To reduce the development of drug-resistant bacteria and maintain the effectiveness of DIFICID and other antibacterial drugs, DIFICID should be used only to treat infections that are proven or strongly suspected to be caused by C. difficile. When culture and susceptibility information are available, they should be considered in selecting or modifying antibacterial therapy. In the absence of such data, local epidemiology and susceptibility patterns may contribute to the empiric selection of therapy.

2 DOSAGE AND ADMINISTRATION

2.1 Important Administration Instructions

DIFICID is available for oral administration as 200 mg tablets and as granules for oral suspension (40 mg/mL (200 mg/5 mL) when reconstituted). DIFICID is administered orally with or without food.

2.2 Adult Patients

The recommended dosage for adults is one 200 mg DIFICID tablet orally twice daily for 10 days.

2.3 Pediatric Patients (6 Months to Less than 18 Years of Age)

Tablets

The recommended dosage for pediatric patients weighing at least 12.5 kg and able to swallow tablets is one 200 mg DIFICID tablet administered orally twice daily for 10 days. If unable to swallow tablets, pediatric patients may be dosed with DIFICID oral suspension as recommended in Table 1 below.

Oral Suspension

The recommended dosage for pediatric patients based on weight are shown in Table 1. Administer DIFICID oral suspension orally twice daily for 10 days using an oral dosing syringe [see Dosage and Administration (2.4)].

Table 1: Recommended Dosage of DIFICID Oral Suspension in Pediatric Patients, Based on Weight
Body Weight | Dose Administered Twice Daily | Volume of 40 mg/mL Suspension to be Administered Orally Twice Daily
4 kg to less than 7 kg | 80 mg | 2 mL
7 kg to less than 9 kg | 120 mg | 3 mL
9 kg to less than 12.5 kg | 160 mg | 4 mL
12.5 kg and above | 200 mg | 5 mL

2.4 Preparation and Administration of DIFICID Oral Suspension

Preparation

1. Shake the glass bottle to ensure the granules move around freely and no caking has occurred.
2. Measure 130 mL of purified water, add to the glass bottle, and cap tightly.
3. Hold bottle in a horizontal position and shake bottle vigorously in that position for at least 2 minutes.
4. Verify that a homogeneous suspension is obtained. If not, repeat the shaking step.
5. Once a homogeneous suspension is visually confirmed, shake an additional 30 seconds.
6. Let bottle stand for 1 minute.
7. Verify that the suspension is still homogeneous. If not, repeat steps 3 through 6.
8. Once reconstituted, DIFICID oral suspension is white to yellowish white in color.
9. Write discard date (current date plus 12 days) on the bottle [see How Supplied/Storage and Handling (16.1, 16.2)].

Storage of Reconstituted Oral Suspension

- Store the reconstituted oral suspension in a refrigerator [between 36°F-46°F (2°C-8°C)] for up to 12 days. Discard after 12 days.

Administration

1. Remove bottle from refrigerator 15 minutes prior to each administration.
2. Shake vigorously until suspension has an even consistency.
3. Remove cap, then administer orally with or without food using an oral dosing syringe.
4. Between doses, replace cap and store in a refrigerator.

3 DOSAGE FORMS AND STRENGTHS

DIFICID tablets

200 mg white to off-white film-coated, oblong tablets; each tablet is debossed with "FDX" on one side and "200" on the other side.

DIFICID for oral suspension

White to yellowish white granules; following reconstitution, each mL of white to yellowish white oral suspension contains 40 mg of fidaxomicin (200 mg of fidaxomicin per 5 mL).

4 CONTRAINDICATIONS

DIFICID is contraindicated in patients who have known hypersensitivity to fidaxomicin or any other ingredient in DIFICID [see Warnings and Precautions (5.1)].

5 WARNINGS AND PRECAUTIONS

5.1 Hypersensitivity Reactions

Acute hypersensitivity reactions, including dyspnea, rash, pruritus, and angioedema of the mouth, throat, and face have been reported with DIFICID. If a severe hypersensitivity reaction occurs, DIFICID should be discontinued and appropriate therapy should be instituted.

Some patients with hypersensitivity reactions to DIFICID also reported a history of allergy to other macrolides. Physicians prescribing DIFICID to patients with a known macrolide allergy should be aware of the possibility of hypersensitivity reactions.

5.2 Not for Use in Infections Other than C. difficile-Associated Diarrhea

DIFICID is not expected to be effective for the treatment of other types of infections due to minimal systemic absorption of fidaxomicin [see Clinical Pharmacology (12.3)]. DIFICID has not been studied for the treatment of infections other than CDAD. DIFICID should only be used for the treatment of CDAD.

5.3 Development of Drug-Resistant Bacteria

Prescribing DIFICID in the absence of proven or strongly suspected C. difficile infection is unlikely to provide benefit to the patient and increases the risk of the development of drug-resistant bacteria.

6 ADVERSE REACTIONS

6.1 Clinical Trials Experience

Because clinical trials are conducted under widely varying conditions, adverse reaction rates observed in the clinical trials of a drug cannot be directly compared to rates in the clinical trials of another drug and may not reflect the rates observed in practice.

Adults

The safety of DIFICID 200 mg tablets taken twice a day for 10 days was evaluated in 564 adult patients with CDAD in two active-controlled trials with 86.7% of patients receiving a full course of treatment.

Thirty-three adult patients receiving DIFICID (5.9%) withdrew from trials as a result of adverse reactions (AR). The types of AR resulting in withdrawal from the study varied considerably. Vomiting was the primary adverse reaction leading to discontinuation of dosing; this occurred at an incidence of 0.5% in both the DIFICID and vancomycin patients in Phase 3 trials. The most common selected adverse reactions occurring in ≥2% of adult patients treated with DIFICID are listed in Table 2.

Table 2: Selected Adverse Reactions with an Incidence of ≥2% Reported in DIFICID-Treated Adult Patients in Controlled Trials
System Organ Class | DIFICID (N=564) | Vancomycin (N=583)
Adverse Reaction | n (%) | n (%)
Blood and Lymphatic System Disorders
Anemia | 14 (2%) | 12 (2%)
Neutropenia | 14 (2%) | 6 (1%)
Gastrointestinal Disorders
Nausea | 62 (11%) | 66 (11%)
Vomiting | 41 (7%) | 37 (6%)
Abdominal Pain | 33 (6%) | 23 (4%)
Gastrointestinal Hemorrhage | 20 (4%) | 12 (2%)

The following adverse reactions were reported in <2% of adult patients taking DIFICID tablets in controlled trials:

Gastrointestinal Disorders: abdominal distension, abdominal tenderness, dyspepsia, dysphagia, flatulence, intestinal obstruction, megacolon

Investigations: increased blood alkaline phosphatase, decreased blood bicarbonate, increased hepatic enzymes, decreased platelet count

Metabolism and Nutrition Disorders: hyperglycemia, metabolic acidosis

Skin and Subcutaneous Tissue Disorders: drug eruption, pruritus, rash

Pediatrics

The safety of DIFICID in pediatric patients 6 months to less than 18 years of age was evaluated in a Phase 2 single-arm trial in 38 patients and a Phase 3 randomized, active-controlled trial in 98 patients treated with DIFICID and 44 patients treated with vancomycin [see Clinical Studies (14.2)]. In both studies, patients received DIFICID orally twice daily for 10 days. Patients <2 years of age, or weighing <12.5 kg, or unable to swallow tablets received weight-based doses of DIFICID oral suspension. Patients weighing at least 12.5 kg and able to swallow tablets received the 200 mg DIFICID tablet. The age range in the Phase 2 trial was 11 months to 17 years and in the Phase 3 trial was 1 month to 17 years (one patient was less than 6 months of age).

One death occurred in the Phase 2 single-arm trial. In the Phase 3 trial, there were 3 deaths in DIFICID-treated patients and no deaths in vancomycin-treated patients during the study period (40 days). All deaths occurred in patients less than 2 years of age and appeared to be related to underlying comorbidities [see Clinical Studies (14.2)].

Treatment discontinuation due to adverse reactions occurred in 7.9% (3/38) of patients in the Phase 2 trial, and in 1% (1/98) and 2.3% (1/44) of DIFICID- and vancomycin-treated patients, respectively, in the Phase 3 trial. The most common selected adverse reactions occurring in ≥5% of pediatric patients treated with DIFICID in the Phase 3 trial are listed in Table 3.

Table 3: Selected Adverse Reactions with an Incidence of ≥5% Reported in DIFICID-Treated Pediatric Patients in the Controlled Trial
System Organ Class | DIFICID (N=98) | Vancomycin (N=44)
Adverse Reaction | n (%) | n (%)
Gastrointestinal Disorders
Abdominal pain [Includes abdominal pain, abdominal pain lower, and abdominal pain upper] | 8 (8.2) | 9 (20.5)
Vomiting | 7 (7.1) | 6 (13.6)
Diarrhea | 7 (7.1) | 5 (11.4)
Constipation | 5 (5.1) | 1 (2.3)
General Disorders and Administration Site Conditions
Pyrexia | 13 (13.3) | 10 (22.7)
Investigations
Aminotransferases increased [Includes alanine aminotransferase increased, aspartate aminotransferase increased, and hepatic enzyme increased] | 5 (5.1) | 1 (2.3)
Skin and Subcutaneous Tissue Disorders
Rash [Includes rash, rash follicular, rash maculo-papular, and exfoliative rash] | 5 (5.1) | 1 (2.3)

The following adverse reactions were reported in <5% of pediatric patients taking DIFICID in clinical trials:

Skin and Subcutaneous Tissue Disorders: urticaria, pruritus

6.2 Post Marketing Experience

The following adverse reactions have been identified during post-approval use of DIFICID. Because these reactions are reported voluntarily from a population of uncertain size, it is not always possible to reliably estimate their frequency or establish a causal relationship to drug exposure.

Hypersensitivity reactions (dyspnea, angioedema, rash, pruritus)

7 DRUG INTERACTIONS

Fidaxomicin and its main metabolite, OP-1118, are substrates of the efflux transporter, P-glycoprotein (P-gp), which is expressed in the gastrointestinal tract.

7.1 Cyclosporine

Cyclosporine is an inhibitor of multiple transporters, including P-gp. When cyclosporine was co-administered with DIFICID, plasma concentrations of fidaxomicin and OP-1118 were significantly increased but remained in the ng/mL range [see Clinical Pharmacology (12.3)]. Concentrations of fidaxomicin and OP-1118 may also be decreased at the site of action (i.e., gastrointestinal tract) via P-gp inhibition; however, concomitant P-gp inhibitor use had no attributable effect on safety or treatment outcome of fidaxomicin-treated adult patients in controlled clinical trials. Based on these results, fidaxomicin may be co-administered with P-gp inhibitors and no dose adjustment is recommended.

8 USE IN SPECIFIC POPULATIONS

8.1 Pregnancy

Risk Summary

The limited available data on use of DIFICID in pregnant women are insufficient to inform any drug-associated risk for major birth defects, miscarriage or adverse maternal or fetal outcomes. Embryo-fetal reproduction studies in rats and rabbits dosed intravenously during organogenesis revealed no evidence of harm to the fetus at fidaxomicin and OP-1118 (its main metabolite) exposures 65-fold or higher than the clinical exposure at the DIFICID recommended dose [see Data].

The estimated background risk of major birth defects and miscarriage for the indicated populations is unknown. All pregnancies have a background risk of birth defect, loss, or other adverse outcomes. In the U.S. general population, the estimated background risk of major birth defects and miscarriage in clinically recognized pregnancies is 2 to 4% and 15 to 20%, respectively.

Data

Animal Data

In pregnant rats, fidaxomicin was administered intravenously at doses of 4, 8, and 15 mg/kg/day from gestation day 6 through 17 (during the period of organogenesis). No embryo/fetal effects were noted in this study at exposures (AUC) 193-fold higher for fidaxomicin, and 65-fold higher for OP-1118 than the clinical exposure at the DIFICID recommended dose.

In pregnant rabbits, fidaxomicin was administered intravenously at doses of 2, 4, and 7.5 mg/kg/day from gestation day 6 through 18 (during the period of organogenesis). No embryo/fetal effects were noted in this study at exposures 66-fold higher for fidaxomicin, and 245-fold higher for OP-1118 than the clinical exposure at the DIFICID recommended dose.

8.2 Lactation

Risk Summary

There is no information on the presence of fidaxomicin or its main metabolite, OP-1118, in human milk, the effects on the breastfed infant, or the effects on milk production. The developmental and health benefits of breastfeeding should be considered along with the mother's clinical need for DIFICID and any potential adverse effects on the breastfed infant from DIFICID or from the underlying maternal condition.

8.4 Pediatric Use

The safety and effectiveness of DIFICID for the treatment of CDAD have been established in pediatric patients 6 months to less than 18 years of age. Use of DIFICID in these age groups is supported by evidence from adequate and well-controlled trials of DIFICID in adults with CDAD and pharmacokinetic, safety and efficacy data from pediatric trials [see Clinical Pharmacology (12.3), Clinical Studies (14.2)]. No new safety signals associated with the use of DIFICID in pediatric patients were identified in the pediatric trials [see Adverse Reactions (6.1)].

The safety and effectiveness of DIFICID have not been established in pediatric patients younger than 6 months of age.

8.5 Geriatric Use

Of the total number of patients in controlled trials of DIFICID, 50% were 65 years of age and over, while 31% were 75 and over. No overall differences in safety or effectiveness of DIFICID compared to vancomycin were observed between these subjects and younger subjects.

In controlled trials, elderly patients (≥65 years of age) had higher plasma concentrations of fidaxomicin and its main metabolite, OP-1118, versus non-elderly patients (<65 years of age) [see Clinical Pharmacology (12.3)]. However, greater exposures in elderly patients were not considered to be clinically significant. No dose adjustment is recommended for elderly patients.

10 OVERDOSAGE

No cases of acute overdose have been reported in humans. No drug-related adverse effects were seen in dogs dosed with fidaxomicin tablets at 9600 mg/day (over 100 times the human dose, scaled by weight) for 3 months.

11 DESCRIPTION

DIFICID (fidaxomicin) is a macrolide antibacterial drug for oral administration. Its CAS chemical name is Oxacyclooctadeca-3,5,9,13,15-pentaen-2-one, 3-[[[6-deoxy-4-O-(3,5-dichloro-2-ethyl-4,6-dihydroxybenzoyl)-2-O-methyl-β-D-mannopyranosyl]oxy]methyl]-12-[[6-deoxy-5-C-methyl-4-O-(2-methyl-1-oxopropyl)-β-D-lyxo-hexopyranosyl]oxy]-11-ethyl-8-hydroxy-18-[(1R)-1-hydroxyethyl]-9,13,15-trimethyl-, (3E,5E,8S,9E,11S,12R,13E,15E,18S)-. The structural formula of fidaxomicin is shown in Figure 1.

Figure 1: Structural Formula of Fidaxomicin

DIFICID tablets are film-coated and contain 200 mg of fidaxomicin per tablet and the following inactive ingredients: butylated hydroxytoluene, hydroxypropyl cellulose, lecithin (soy), magnesium stearate, microcrystalline cellulose, polyethylene glycol, polyvinyl alcohol, pregelatinized starch, sodium starch glycolate, talc, and titanium dioxide.

DIFICID for oral suspension is supplied as granules in bottles containing 5.45 g of fidaxomicin (40 mg of fidaxomicin per mL after reconstitution) and the following inactive ingredients: citric acid, microcrystalline cellulose, mixed berry flavor, sodium benzoate, sodium citrate, sodium starch glycolate, sucralose, and xanthan gum.

12 CLINICAL PHARMACOLOGY

12.1 Mechanism of Action

Fidaxomicin is an antibacterial drug [see Microbiology (12.4)].

12.2 Pharmacodynamics

Fidaxomicin acts locally in the gastrointestinal tract on C. difficile. In a dose-ranging trial (N=48) of fidaxomicin using 50 mg, 100 mg, and 200 mg twice daily for 10 days, a dose-response relationship was observed for efficacy.

12.3 Pharmacokinetics

The pharmacokinetic parameters of fidaxomicin and its main metabolite OP-1118 following a single dose of 200 mg in healthy adult males (N=14) are summarized in Table 4.

Table 4: Mean (± Standard Deviation) Pharmacokinetic Parameters of Fidaxomicin 200 mg in Healthy Adult Males
Parameter | Fidaxomicin |  | OP-1118
 | N | Value | N | Value
Cmax (ng/mL) | 14 | 5.20 ± 2.81 | 14 | 12.0 ± 6.06
Tmax (h) [Tmax, reported as median (range). Cmax, maximum observed concentration; Tmax, time to maximum observed concentration; AUC0-t, area under the concentration-time curve from time 0 to the last measured concentration; AUC0-∞, area under the concentration-time curve from time 0 to infinity; t1/2, elimination half-life] | 14 | 2.00 (1.00-5.00) | 14 | 1.02 (1.00-5.00)
AUC0-t (ng-h/mL) | 14 | 48.3 ± 18.4 | 14 | 103 ± 39.4
AUC0-∞ (ng-h/mL) | 9 | 62.9 ± 19.5 | 10 | 118 ± 43.3
t1/2 (h) | 9 | 11.7 ± 4.80 | 10 | 11.2 ± 3.01

Absorption

Fidaxomicin has minimal systemic absorption following oral administration, with plasma concentrations of fidaxomicin and OP-1118 in the ng/mL range at the therapeutic dose. In fidaxomicin-treated patients from controlled trials, plasma concentrations of fidaxomicin and OP-1118 obtained within the Tmax window (1-5 hours) were approximately 2- to 6-fold higher than Cmax values in healthy adults. Following administration of DIFICID 200 mg twice daily for 10 days, OP-1118 plasma concentrations within the Tmax window were approximately 50%-80% higher than on Day 1, while concentrations of fidaxomicin were similar on Days 1 and 10.

In a food-effect study involving administration of DIFICID to healthy adults (N=28) with a high-fat meal versus under fasting conditions, Cmax of fidaxomicin and OP-1118 decreased by 21.5% and 33.4%, respectively, while AUC0-t remained unchanged. This decrease in Cmax is not considered clinically significant, and thus, DIFICID may be administered with or without food.

Distribution

Fidaxomicin is mainly confined to the gastrointestinal tract following oral administration. In selected patients (N=8) treated with DIFICID 200 mg twice daily for 10 days from controlled trials, fecal concentrations of fidaxomicin and OP-1118 obtained within 24 hours of the last dose ranged from 639-2710 µg/g and 213-1210 µg/g, respectively. In contrast, plasma concentrations of fidaxomicin and OP-1118 within the Tmax window (1-5 hours) ranged 2-179 ng/mL and 10-829 ng/mL, respectively.

Elimination

Metabolism

Fidaxomicin is primarily transformed by hydrolysis at the isobutyryl ester to form its main and microbiologically active metabolite, OP-1118. Metabolism of fidaxomicin and formation of OP-1118 are not dependent on cytochrome P450 (CYP) enzymes.

At the therapeutic dose, OP-1118 was the predominant circulating compound in healthy adults, followed by fidaxomicin.

Excretion

Fidaxomicin is mainly excreted in feces. In one trial of healthy adults (N=11), more than 92% of the dose was recovered in the stool as fidaxomicin and OP-1118 following single doses of 200 mg and 300 mg. In another trial of healthy adults (N=6), 0.59% of the dose was recovered in urine as OP-1118 only following a single dose of 200 mg.

Specific Populations

Geriatric Patients

In controlled trials of patients treated with DIFICID 200 mg twice daily for 10 days, mean and median values of fidaxomicin and OP-1118 plasma concentrations within the Tmax window (1-5 hours) were approximately 2- to 4-fold higher in elderly patients (≥65 years of age) versus non-elderly patients (<65 years of age). Despite greater exposures in elderly patients, fidaxomicin and OP-1118 plasma concentrations remained in the ng/mL range [see Use in Specific Populations (8.5)].

Pediatric Patients

Similar to adults, fidaxomicin has minimal systemic absorption following oral administration across all age groups in pediatric patients. Plasma concentrations remained in the ng/mL range at the therapeutic dose in pediatric patients with mean (± standard deviation) plasma concentrations of 39.41 (±62.15) ng/mL of fidaxomicin and 116.64 (±259.10) ng/mL of OP-1118 at 1 to 5 hours post-dose.

Male and Female Patients

Plasma concentrations of fidaxomicin and OP-1118 within the Tmax window (1-5 hours) did not vary by gender in patients treated with DIFICID 200 mg twice daily for 10 days from controlled trials. No dose adjustment is recommended based on gender.

Patients with Renal Impairment

In controlled trials of patients treated with DIFICID 200 mg twice daily for 10 days, plasma concentrations of fidaxomicin and OP-1118 within the Tmax window (1-5 hours) did not vary by severity of renal impairment (based on creatinine clearance) between mild (51-79 mL/min), moderate (31-50 mL/min), and severe (≤30 mL/min) categories. No dose adjustment is recommended based on renal function.

Patients with Hepatic Impairment

The impact of hepatic impairment on the pharmacokinetics of fidaxomicin has not been evaluated. Because fidaxomicin and OP-1118 do not appear to undergo significant hepatic metabolism, elimination of fidaxomicin and OP-1118 is not expected to be significantly affected by hepatic impairment.

Drug Interaction Studies

In vivo studies were conducted to evaluate intestinal drug-drug interactions of fidaxomicin as a P-gp substrate, P-gp inhibitor, and inhibitor of major CYP enzymes expressed in the gastrointestinal tract (CYP3A4, CYP2C9, and CYP2C19).

Table 5 summarizes the impact of a co-administered drug (P-gp inhibitor) on the pharmacokinetics of fidaxomicin [see Drug Interactions (7.1)].

Table 5: Pharmacokinetic Parameters of Fidaxomicin and OP-1118 in the Presence of a Co-Administered Drug
Parameter | Cyclosporine 200 mg + Fidaxomicin 200 mg [Cyclosporine was administered 1 hour before fidaxomicin.] (N=14) |  | Fidaxomicin 200 mg Alone (N=14) |  | Mean Ratio of Parameters With/Without Co-Administered Drug (90% CI [CI - confidence interval]) No Effect = 1.00
 | N | Mean | N | Mean | Mean Ratio of Parameters With/Without Co-Administered Drug (90% CI [CI - confidence interval]) No Effect = 1.00
Fidaxomicin
Cmax (ng/mL) | 14 | 19.4 | 14 | 4.67 | 4.15 (3.23-5.32)
AUC0-∞ (ng-h/mL) | 8 | 114 | 9 | 59.5 | 1.92 (1.39-2.64)
OP-1118
Cmax (ng/mL) | 14 | 100 | 14 | 10.6 | 9.51 (6.93-13.05)
AUC0-∞ (ng-h/mL) | 12 | 438 | 10 | 106 | 4.11 (3.06-5.53)

Fidaxomicin had no significant impact on the pharmacokinetics of the following co-administered drugs: digoxin (P-gp substrate), midazolam (CYP3A4 substrate), warfarin (CYP2C9 substrate), and omeprazole (CYP2C19 substrate). No dose adjustment is warranted when fidaxomicin is co-administered with substrates of P-gp or CYP enzymes.

12.4 Microbiology

Mechanism of Action

Fidaxomicin is a fermentation product obtained from the Actinomycete Dactylosporangium aurantiacum. Fidaxomicin is a macrolide antibacterial drug that inhibits RNA synthesis by binding to RNA polymerases. Fidaxomicin is bactericidal against C. difficile in vitro, and demonstrates a post-antibiotic effect vs. C. difficile of 6-10 hrs.

Resistance

Fidaxomicin demonstrates no in vitro cross-resistance with other classes of antibacterial drugs. In vitro studies indicate a low frequency of spontaneous resistance to fidaxomicin in C. difficile (ranging from <1.4 × 10^-9 to 12.8 × 10^-9). A specific mutation (Val-ll43-Gly) in the beta subunit of RNA polymerase is associated with reduced susceptibility to fidaxomicin. This mutation was created in the laboratory and seen during clinical trials in a C. difficile isolate obtained from an adult subject treated with DIFICID who had recurrence of CDAD. The fidaxomicin minimum inhibitory concentration (MIC) of the C. difficile isolate from this subject increased from a baseline of 0.06 µg/mL to 16 µg/mL at the time of CDAD recurrence.

Interaction With Other Antimicrobials

Fidaxomicin and its main metabolite OP-1118 do not exhibit any antagonistic interaction with other classes of antibacterial drugs. Synergistic interactions of fidaxomicin and OP-1118 have been observed in vitro with rifampin and rifaximin against C. difficile.

Antimicrobial Activity

Fidaxomicin has been shown to be active against most isolates of Clostridioides (formerly Clostridium) difficile, both in vitro and in clinical infections [see Indications and Usage (1)].

Susceptibility Testing

For specific information regarding susceptibility test interpretive criteria, and associated test methods and quality control standards recognized by FDA for this drug, please see: https://www.fda.gov/STIC .

13 NONCLINICAL TOXICOLOGY

13.1 Carcinogenesis, Mutagenesis, Impairment of Fertility

Long-term carcinogenicity studies have not been conducted to evaluate the carcinogenic potential of fidaxomicin.

Neither fidaxomicin nor OP-1118 was mutagenic in the Ames assay. Fidaxomicin was also negative in the rat micronucleus assay. However, fidaxomicin was clastogenic in Chinese hamster ovary cells.

Fidaxomicin did not affect the fertility of male and female rats at intravenous doses of 6.3 mg/kg. The exposure (AUC0-t) was approximately 100 times that in humans.

14 CLINICAL STUDIES

14.1 Clinical Studies of DIFICID in Adult Patients with CDAD

In two randomized, double-blinded trials, a non-inferiority design was utilized to demonstrate the efficacy of DIFICID (200 mg tablets twice daily for 10 days) compared to vancomycin (125 mg four times daily for 10 days) in adults with CDAD.

Enrolled patients were 18 years of age or older and received no more than 24 hours of pretreatment with vancomycin or metronidazole. CDAD was defined by >3 unformed bowel movements (or >200 mL of unformed stool for subjects having rectal collection devices) in the 24 hours before randomization, and presence of either C. difficile toxin A or B in the stool within 48 hours of randomization. Enrolled patients had either no prior CDAD history or only one prior CDAD episode in the past three months. Subjects with life-threatening/fulminant infection, hypotension, septic shock, peritoneal signs, significant dehydration, or toxic megacolon were excluded.

The demographic profile and baseline CDAD characteristics of enrolled subjects were similar in the two trials. Patients had a median age of 64 years, were mainly white (90%), female (58%), and inpatients (63%). The median number of bowel movements per day was 6, and 37% of subjects had severe CDAD (defined as 10 or more unformed bowel movements per day or WBC ≥15000/mm^3). Diarrhea alone was reported in 45% of patients and 84% of subjects had no prior CDAD episode.

The primary efficacy endpoint was the clinical response rate at the end of treatment, based upon improvement in diarrhea or other symptoms such that, in the investigator's judgment, further CDAD treatment was not needed. An additional efficacy endpoint was sustained clinical response 25 days after the end of treatment. Sustained response was evaluated only for patients who were clinical successes at the end of treatment. Sustained response was defined as clinical response at the end of treatment, and survival without proven or suspected CDAD recurrence through 25 days beyond the end of treatment.

The results for clinical response at the end of treatment in both trials, shown in Table 6, indicate that DIFICID is non-inferior to vancomycin based on the 95% confidence interval (CI) lower limit being greater than the non-inferiority margin of -10%.

The results for sustained clinical response at the end of the follow-up period, also shown in Table 6, indicate that DIFICID is superior to vancomycin on this endpoint. Since clinical success at the end of treatment and mortality rates were similar across treatment arms (approximately 6% in each group), differences in sustained clinical response were due to lower rates of proven or suspected CDAD during the follow-up period in DIFICID patients.

Table 6: Clinical Response Rates at End-of-Treatment and Sustained Response at 25 days Post-Treatment in Adult Patients
 | Clinical Response at End of Treatment |  |  | Sustained Response at 25 days Post-Treatment
 | DIFICID % (N) | Vancomycin % (N) | Difference (95% CI) [Confidence interval (CI) was derived using Wilson's score method. Approximately 5%-9% of the data in each trial and treatment arm were missing sustained response information and were imputed using multiple imputation method.] | DIFICID % (N) | Vancomycin % (N) | Difference (95% CI)
Trial 1 | 88% (N=289) | 86% (N=307) | 2.6% (-2.9%, 8.0%) | 70% (N=289) | 57% (N=307) | 12.7% (4.4%, 20.9%)
Trial 2 | 88% (N=253) | 87% (N=256) | 1.0% (-4.8%, 6.8%) | 72% (N=253) | 57% (N=256) | 14.6% (5.8%, 23.3%)

Restriction Endonuclease Analysis (REA) was used to identify C. difficile baseline isolates in the BI group, isolates associated with increasing rates and severity of CDAD in the US in the years prior to the clinical trials. Similar rates of clinical response at the end of treatment and proven or suspected CDAD during the follow-up period were seen in fidaxomicin-treated and vancomycin-treated patients infected with a BI isolate. However, DIFICID did not demonstrate superiority in sustained clinical response when compared with vancomycin (Table 7).

Table 7: Sustained Clinical Response at 25 Days after Treatment by C. difficile REA Group at Baseline in Adult Patients
Trial 1
Initial C. difficile Group | DIFICID n/N (%) | Vancomycin n/N (%) | Difference (95% CI) [Interaction test between the effect on sustained response rate and BI versus non-BI isolates using logistic regression (p-values: trial 1: 0.009; trial 2: 0.29). Approximately 25% of the mITT population were missing data for REA group. Confidence intervals (CI) were derived using Wilson's score method.]
BI Isolates | 44/76 (58%) | 52/82 (63%) | -5.5% (-20.3%, 9.5%)
Non-BI Isolates | 105/126 (83%) | 87/131 (66%) | 16.9% (6.3%, 27.0%)
Trial 2
Initial C. difficile Group | DIFICID n/N (%) | Vancomycin n/N (%) | Difference (95% CI)
BI Isolates | 42/65 (65%) | 31/60 (52%) | 12.9% (-4.2%, 29.2%)
Non-BI Isolates | 109/131 (83%) | 77/121 (64%) | 19.6% (8.7%, 30.0%)

14.2 Clinical Studies of DIFICID in Pediatric Patients with CDAD

The safety and efficacy of DIFICID in pediatric patients 6 months to less than 18 years of age was investigated in a Phase 3, multicenter, investigator-blinded, randomized, comparative trial (NCT02218372). In this trial, 148 patients were randomized, of whom 142 received either DIFICID or vancomycin in a 2:1 ratio. Randomized patients were stratified by age group as follows: 30 aged 6 months to <2 years, 49 aged 2 to <6 years, 40 aged 6 to <12 years, and 29 aged 12 to <18 years (one patient <6 months of age was enrolled in the trial). Treatment arms were balanced regarding demographics and other baseline characteristics.

Clinical response for patients <2 years of age was defined as the absence of watery stools for at least 2 consecutive days while on treatment and the patient remained well with no requirement for further CDAD therapy through 2 days after completing treatment as assessed by the Investigator. Clinical response for patients ≥2 to <18 years of age was defined as <3 unformed bowel movements for at least 2 consecutive days while on treatment and the patient remained well with no requirement for further CDAD therapy through 2 days after completing treatment as assessed by the Investigator. Sustained clinical response was defined as the proportion of treated patients with confirmed clinical response and no CDAD recurrence through 30 days after end of treatment. The clinical response and sustained clinical response overall and by age groups are presented in Table 8.

Table 8: Clinical Response and Sustained Response Overall and by Age Group in Pediatric Patients
 | Clinical Response |  |  | Sustained Response at 30 days Post-Treatment
 | DIFICID n/N (%) | Vancomycin n/N (%) | Difference (95% CI) | DIFICID n/N (%) | Vancomycin n/N (%) | Difference (95% CI)
Overall | 76/98 (77.6) | 31/44 (70.5) | 7.5 (-7.4, 23.9) | 67/98 (68.4) | 22/44 (50.0) | 18.4 (1.5, 35.3)
<2 years | 13/20 (65.0) | 9/10 (90.0) |  | 11/20 (55.0) | 7/10 (70.0)
≥2 to <6 years | 25/32 (78.1) | 12/16 (75.0) |  | 21/32 (65.6) | 8/16 (50.0)
≥6 to <12 years | 23/26 (88.5) | 5/10 (50.0) |  | 22/26 (84.6) | 4/10 (40.0)
≥12 to <18 years | 15/20 (75.0) | 5/8 (62.5) |  | 13/20 (65.0) | 3/8 (37.5)

16 HOW SUPPLIED/STORAGE AND HANDLING

16.1 How Supplied

Tablets

DIFICID tablets are white to off-white film-coated, oblong tablets containing 200 mg of fidaxomicin per tablet; each tablet is debossed with "FDX" on one side and "200" on the other side.

DIFICID tablets are supplied as bottles of 20 tablets (NDC 52015-080-01).

Granules for Oral Suspension

DIFICID granules for oral suspension are white to yellowish white.

DIFICID granules for oral suspension (NDC 52015-700-22) is supplied as 150 mL amber glass bottles of 9.53 g of granules that contain 5.45 g of fidaxomicin. Each glass bottle has a child-resistant cap and is sealed in a laminated aluminum foil pouch. After reconstitution, the total oral suspension volume is 136 mL. Discard unused suspension after 12 days. The concentration of fidaxomicin is 40 mg/mL (200 mg per 5 mL) in the reconstituted oral suspension.

16.2 Storage

Tablets

Store DIFICID tablets at 20°C-25°C (68°F-77°F); excursions permitted to 15°C-30°C (59°F-86°F). See USP controlled room temperature. Store in the original bottle.

Granules for oral suspension

Store DIFICID granules for oral suspension at 20°C-25°C (68°F-77°F); excursions permitted to 15°C-30°C (59°F-86°F). Store in the original package. Do not open pouch until time of use.

Once reconstituted, store DIFICID oral suspension refrigerated at 2°C-8°C (36°F-46°F) for up to 12 days. Store capped in the original bottle.

17 PATIENT COUNSELING INFORMATION

Advise the patient to read the FDA-approved patient labeling (Patient Information).

Oral Suspension

Remove the bottle from the refrigerator 15 minutes prior to each administration.

Instruct patients or caregivers to use an oral dosing syringe to correctly measure the prescribed amount of medication. Inform patients or caregivers that oral dosing syringes may be obtained from their pharmacy.

Inform the patients or caregivers that DIFICID oral suspension should be prepared by a healthcare professional. Advise them to contact a healthcare professional for any questions regarding administration of DIFICID oral suspension.

Administration with Food

Inform patients and caregivers that DIFICID tablets and oral suspension may be taken with or without food.

Antibacterial Resistance

Patients should be counseled that antibacterial drugs, including DIFICID, should only be used to treat bacterial infections. They do not treat viral infections (e.g., the common cold). When DIFICID is prescribed to treat a C. difficile infection, patients should be told that, although it is common to feel better early in the course of therapy, the medication should be taken exactly as directed. Skipping doses or not completing the full course of therapy may (1) decrease the effectiveness of the immediate treatment and (2) increase the likelihood that bacteria will develop resistance and will not be treatable by DIFICID or other antibacterial drugs in the future.

Manufactured for: Merck Sharp & Dohme LLC
Rahway, NJ 07065, USA

For patent information: www.msd.com/research/patent

Copyright © 2015-2022 Merck & Co., Inc., Rahway, NJ, USA, and its affiliates.
All rights reserved.

uspi-mk5119-mf-2206r007

Patient Information
DIFICID® (dih-fih-sid)
(fidaxomicin)
tablets, for oral use
DIFICID® (dih-fih-sid)
(fidaxomicin)
for oral suspension

What You Need to Know About Your Medicine

- Before you take DIFICID, be sure you understand what it is for and how to take it.
- If you have questions about DIFICID, ask your doctor or pharmacist.
- Remember that your doctor has prescribed DIFICID only for you. Never give this medicine to anyone else.
- Keep this Patient Information for DIFICID so you can read it again.

What is DIFICID?

DIFICID is an antibiotic medicine used to treat an infection called Clostridioides difficile-associated diarrhea (CDAD) in adults and children 6 months of age and older. Clostridioides difficile (C-diff) is a bacterium that can cause an infection that can damage your colon and cause stomach pain and severe diarrhea.

- DIFICID is not to be used to treat other types of infections in the body.
- Sometimes infections are caused by viruses rather than bacteria. Antibiotic medicines, including DIFICID, do not kill viruses.

It is not known if DIFICID is safe and effective in children under 6 months old.

Who should not take DIFICID?

Do not take DIFICID if you are allergic to fidaxomicin, or any other ingredient in DIFICID. See the end of this Patient Information for a complete list of ingredients in DIFICID.

What should I tell my doctor before taking DIFICID?

Pregnancy

- If you are pregnant or plan to become pregnant, tell your doctor before you take DIFICID.
- It is not known if DIFICID will harm your baby while you are pregnant.
- If you are pregnant, you and your doctor should decide together if you will take DIFICID.

Breastfeeding

- If you are breastfeeding or plan to breastfeed, tell your doctor before you take DIFICID.
- It is not known if DIFICID passes into breast milk.
- If you are breastfeeding, you and your doctor should decide together if you will take DIFICID.

Other Medicines

- Tell your doctor about all of the medicines you take, including prescription and over-the-counter medicines, vitamins, and herbal and dietary supplements.
- Know the medicines you take. Keep a list of your medicines to show your doctor and pharmacist when you get a new medicine.

Allergic Reactions

- See "Who should not take DIFICID?"
- If you are allergic to other kinds of antibiotics called macrolides (for example: azithromycin (Zithromax) or clarithromycin (Biaxin)) or any other ingredient in DIFICID, tell your doctor.
  See the end of this Patient Information for a complete list of ingredients in DIFICID.

How do I take DIFICID?

- Take DIFICID tablets or oral suspension exactly as prescribed by your doctor.
- Take DIFICID twice a day (approximately every 12 hours). For example, if you take your first dose at 8:00 a.m. you should take your second dose at 8:00 p.m.
- You can take DIFICID with or without food.
- If DIFICID oral suspension is prescribed for your child:
  - DIFICID oral suspension is a liquid that your pharmacist will mix before it is given to you.
  - Store DIFICID oral suspension in the refrigerator (see "How should I store DIFICID?").
  - Take the bottle out of the refrigerator 15 minutes before giving the dose to your child.
  - Shake the bottle well before each dose. DIFICID oral suspension should be white to yellowish white.
  - Remove the cap and measure the dose with the oral dosing syringe provided by your pharmacist.
  - Give the dose by mouth to your child using the oral dosing syringe.
  - Put the cap back on the bottle and store in the refrigerator after each dose.
- Do not skip any doses or stop taking DIFICID until you finish your prescribed treatment, even if you begin to feel better, unless you have a serious allergic reaction (see "What are the possible side effects of DIFICID?").
  This will lower the chance that the bacteria will become resistant to DIFICID. If this happens, DIFICID and other antibiotic medicines may not work in the future.

What are the possible side effects of DIFICID?

DIFICID can cause serious side effects, including:

- Allergic reaction. If you get a severe allergic reaction while taking DIFICID, including problems breathing or shortness of breath, rash, itching or hives, or swelling of the mouth, throat, or face, stop taking DIFICID and get emergency medical help right away.

Common side effects of DIFICID include:
The most common side effects of DIFICID in adults include:

- nausea
- vomiting
- stomach pain

- bleeding in the stomach or intestines
- low red blood cell count (anemia)
- low white blood cell count (neutropenia)

The most common side effects of DIFICID in children include:

- fever
- vomiting
- diarrhea
- stomach pain

- constipation
- rash
- high levels of enzymes called aminotransferases in the blood, which may indicate liver damage

Other less common side effects of DIFICID may include:

- swelling of any body part (such as your face, lips, tongue or around your eyes)
- itching

- hives
- bloating
- stomach tenderness
- heartburn
- problems swallowing
- high blood sugar (hyperglycemia)
- abnormal liver tests
- low levels of blood bicarbonate

- passing gas
- intestinal blockage
- serious bowel inflammation (toxic megacolon)
- low platelet count (important for clotting and to control bleeding)
- high levels of acid in your blood (metabolic acidosis)

If you have any side effect that bothers you or does not go away, tell your doctor.

There may be other side effects to DIFICID that are not listed. Call your doctor for medical advice about side effects. You may report side effects to FDA at 1-800-FDA-1088.

How should I store DIFICID?

DIFICID tablets

- Store DIFICID tablets at room temperature between 68°F to 77°F (20°C to 25°C).
- Keep DIFICID in its original bottle until you are ready to take it.

DIFICID for oral suspension

- Store DIFICID oral suspension in the refrigerator between 36°F to 46°F (2°C to 8°C) for up to 12 days. Throw away (discard) any unused DIFICID oral suspension by the date written on the bottle.
- Keep DIFICID in its original child-resistant bottle with the cap on until you are ready to give it to your child.

Keep DIFICID and all medicines out of the reach of children.

General information about the safe and effective use of DIFICID.

Medicines are sometimes prescribed for purposes other than those listed in the Patient Information. Do not take DIFICID for a condition for which it was not prescribed. Do not give DIFICID to other people, even if they have the same symptoms that you have. It may harm them. You can ask your pharmacist or doctor for information about DIFICID that is written for health professionals.

What if I have questions?

- Call your doctor.
- Call the company that makes DIFICID at 1-800-444-2080.
- Go to the website – www.DIFICID.com .
- You can also find the full prescribing information written for doctors at www.DIFICID.com

What are the ingredients in DIFICID?

DIFICID tablets

- Active ingredient: fidaxomicin.
- Inactive ingredients: butylated hydroxytoluene, hydroxypropyl cellulose, lecithin (soy), magnesium stearate, microcrystalline cellulose, polyethylene glycol, polyvinyl alcohol, pregelatinized starch, sodium starch glycolate, talc, and titanium dioxide.

DIFICID for oral suspension

- Active ingredient: fidaxomicin.
- Inactive ingredients: citric acid, microcrystalline cellulose, mixed berry flavor, sodium benzoate, sodium citrate, sodium starch glycolate, sucralose, and xanthan gum.

Manuf. for: Merck Sharp & Dohme LLC
Rahway, NJ 07065, USA

For patent information: www.msd.com/research/patent. The trademarks depicted herein are owned by their respective companies.

Copyright © 2019-2022 Merck & Co., Inc., Rahway, NJ, USA, and its affiliates.
All rights reserved.

usppi-mk5119-mf-2206r002

This Patient Information has been approved by the U.S. Food and Drug Administration.
Revised: 06/2022

PRINCIPAL DISPLAY PANEL - 200 mg Tablet Bottle Carton

NDC 52015-080-01 20 tablets

DIFICID®
(fidaxomicin) tablets

200 mg per tablet

Rx only

PRINCIPAL DISPLAY PANEL - 40 mg/mL Bottle Pouch Carton

NDC 52015-700-22

DIFICID®
(fidaxomicin) for oral suspension

40 mg/mL

MUST BE RECONSTITUTED BY A PHARMACIST
BEFORE DISPENSING

See enclosed package insert for preparation instructions.

For pediatric use
For oral administration only

Each mL contains 40 mg fidaxomicin after reconstitution
with 130 mL purified water. (136 mL total volume
after reconstitution)

Mixed berry flavored Rx only